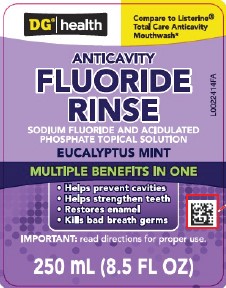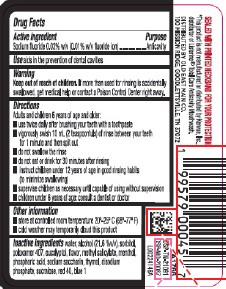 DRUG LABEL: Anticavity
NDC: 55910-163 | Form: MOUTHWASH
Manufacturer: Old East Main Co.
Category: otc | Type: HUMAN OTC DRUG LABEL
Date: 20260302

ACTIVE INGREDIENTS: SODIUM FLUORIDE 0.1 mg/1 mL
INACTIVE INGREDIENTS: WATER; ALCOHOL; SORBITOL; POLOXAMER 407; EUCALYPTOL; METHYL SALICYLATE; MENTHOL, UNSPECIFIED FORM; PHOSPHORIC ACID; SACCHARIN SODIUM; THYMOL; SODIUM PHOSPHATE, DIBASIC, ANHYDROUS; SUCRALOSE; FD&C RED NO. 40; FD&C BLUE NO. 1

DG Health 163.005/163AF-AG
Anticavity Fluoride Rinse

Active ingredient

Sodium fluoride 0.02% w/v (0.01% w/v fluoride ion)

Purpose

Anticavity

Use

aids in the prevention of dental cavities

Warnings

for this product

Keep out of reach of children.

If more than used for rinsing is accidentally swallowed, get medical help or contact a Poison Control Center right away.

Directions

Adults and children 6 years of age and older:

- use twice daily after brushing your teeth with a toothpaste
- vigorously swish 10 mL (2 teaspoonfuls) of rinse between your teeth for 1 minute and then spit out
- do not swallow the rinse
- do not eat or drink for 30 minutes after rinsing
- instruct children under 12 years of age in good rinsing habits (to minimize swallowing)
- supervise children as necessary until capable of using without supervision
- children under 6 years of age: consult a dentist or doctor

Other information

- store at controlled room temperature 20⁰- 25⁰C (68⁰- 77⁰F)
- cold weather may temporarily cloud this product

Inactive ingredients

water, alcohol (21.6 %v/v), sorbitol, poloxamer 407, eucalyptol, flavor, methyl salicylate, menthol, phosphoric acid, sodium saccharin, thymol, disodium phosphate, sucralose, red 40, blue 1

Tamper Evident Statement

SEALED WITH PRINTED NECKBAND FOR YOUR PROTECTION.

Adverse Reaction

DISTRIBUTED BY OLD EAST MAIN CO.

100 MISSION RIDGE, GOODLETTSVILLE, TN 37072

DSP-TN-21091

DSP-MO-20087

Disclaimer

*This product is not manufactured or distributed by Kenvue, Inc., distributor of Listerine®Total Care Anticavity Mouthwash.

Principal Panel Display

DG®health

Compare to Listerine®Total Care Anticavity Mouthwash*

Anticavity

Fluoride

Rinse

Sodium Fluoride and Acidulated Phosphate Topical Solution

Eucalyptus Mint

Multiple Benefits in one

- Helps prevent cavities
- Helps strengthen teeth
- Restores enamel
- Kills bad breath germs

IMPORTANT: read directions for proper use.

250 mL (8.5 FL OZ)